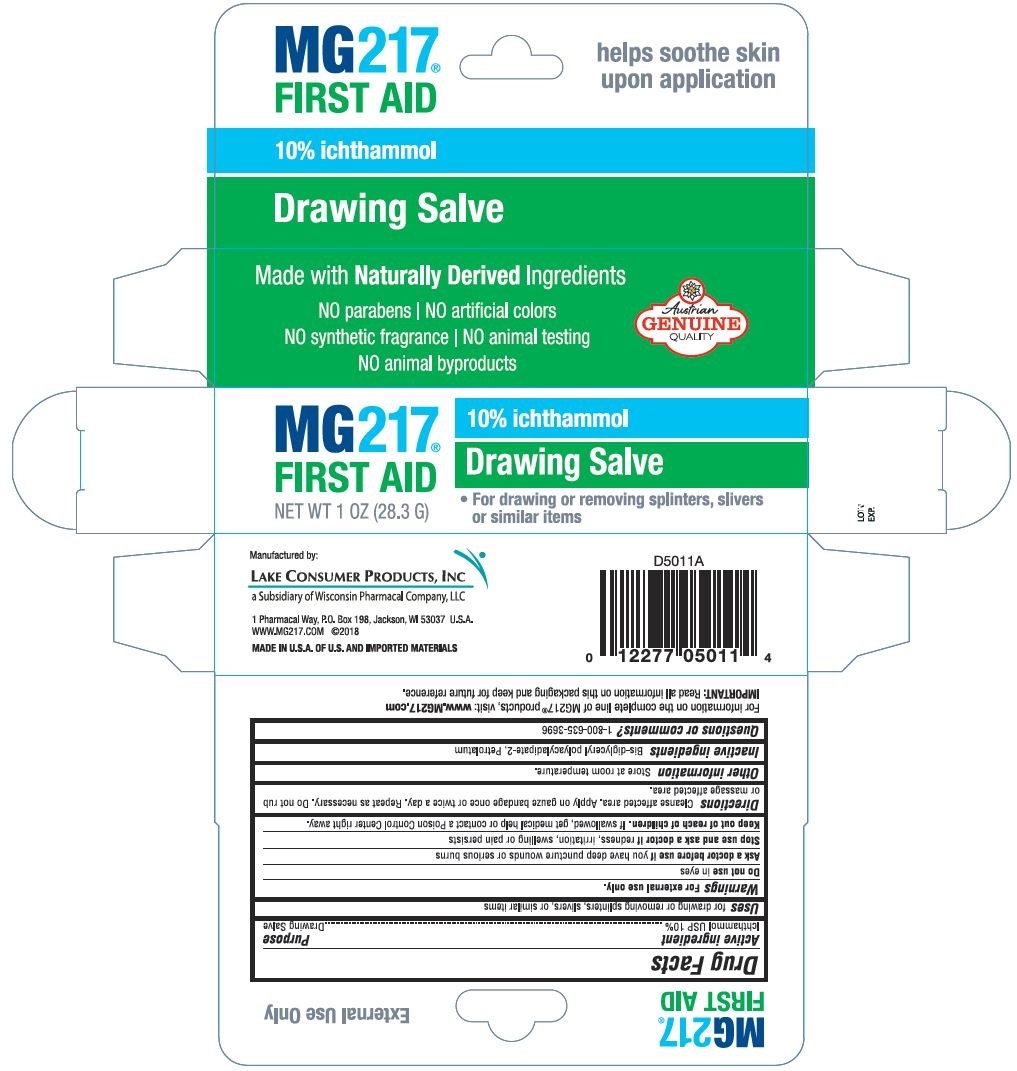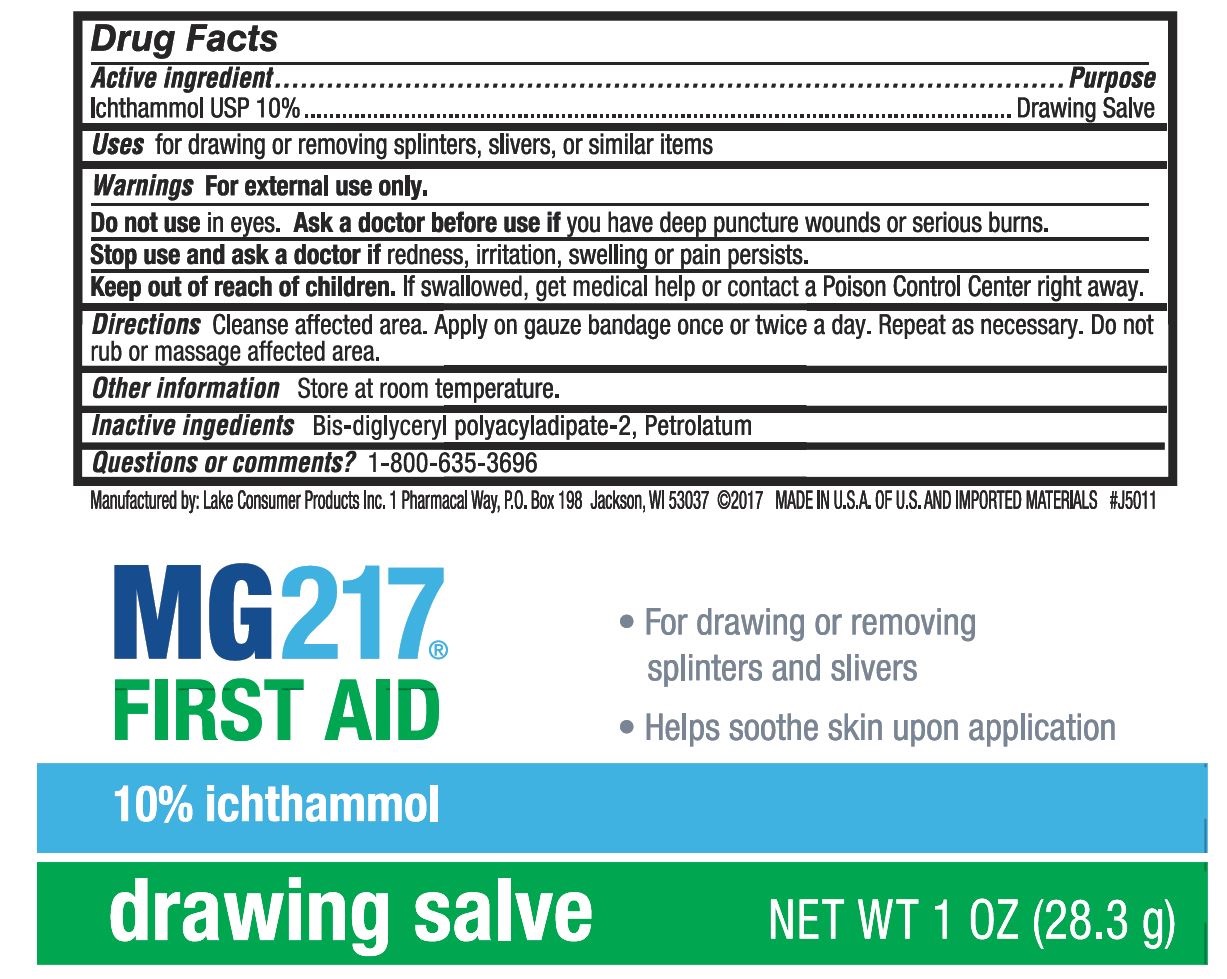 DRUG LABEL: MG217 First Aid Drawing Salve
NDC: 68093-7218 | Form: OINTMENT
Manufacturer: Wisconsin Pharmacal Company
Category: otc | Type: HUMAN OTC DRUG LABEL
Date: 20220113

ACTIVE INGREDIENTS: ICHTHAMMOL 100 mg/1 g
INACTIVE INGREDIENTS: BIS-DIGLYCERYL POLYACYLADIPATE-2; PETROLATUM

MG217 First Aid Drawing Salve

PURPOSE

For drawing or removing splinters, slivers, or similar items

Drug Facts

Active ingredients | Purpose
Ichthammol USP 10% | Drawing Salve

Uses

For drawing or removing splinters, slivers, or similar ijems

Warnings

For external use only

Do not use in eyes.

Ask a doctor before use if you have deep puncture wounds or serious burns.

Stop use and ask a doctor if redness, irritation, swelling or pain persists.

KEEP OUT OF REACH OF CHILDREN

Keep out of reach of chlldren. If swallowed, get medical help or contact a Poison Control Center right away.

Directions

Cleanse affected area. Apply on gauze bandage once or twice a day. Repeat as necessary. Do not rub or massaoe affected area.

Other information

Store at room temperature.

Inactive ingredients

Bis-diglyceryl polyacyladipate-2, Petrolatum

Questions or comments?

1-800-635-3696